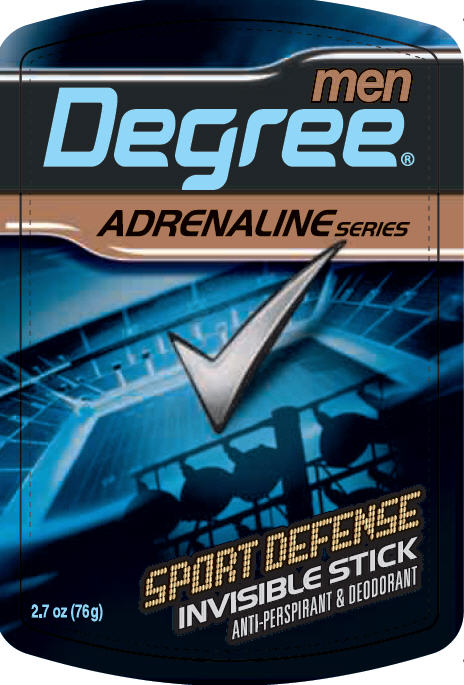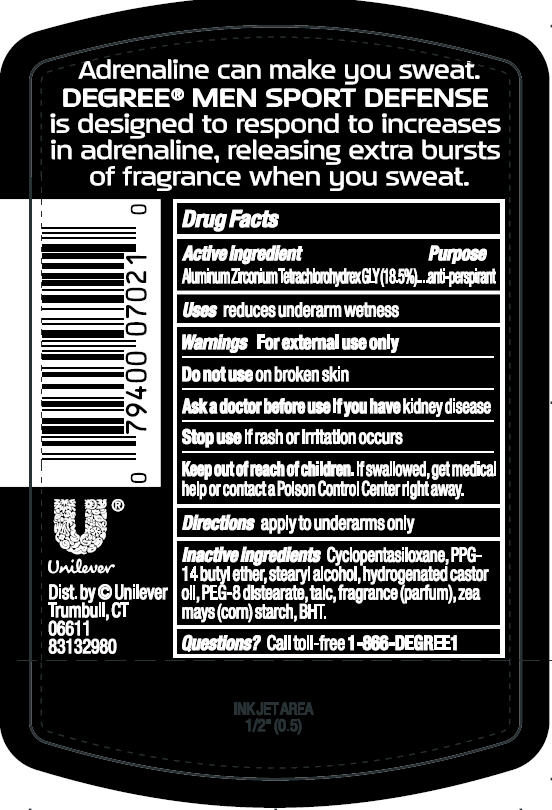 DRUG LABEL: Degree
NDC: 64942-1154 | Form: STICK
Manufacturer: Conopco Inc. d/b/a Unilever
Category: otc | Type: HUMAN OTC DRUG LABEL
Date: 20101222

ACTIVE INGREDIENTS: Aluminum Zirconium Tetrachlorohydrex GLY 18.5 g/100 g
INACTIVE INGREDIENTS: CYCLOMETHICONE 5; PPG-14 BUTYL ETHER; STEARYL ALCOHOL; HYDROGENATED CASTOR OIL; PEG-8 DISTEARATE; TALC; STARCH, CORN; BUTYLATED HYDROXYTOLUENE

Degree Men Adrenaline Sport Defense antiperspirant deodorant

Active Ingredient

Aluminum Zirconium Tetrachlorohydrex GLY (18.5%)

Purpose
antiperspirant

Uses
reduces underarm wetness

Warnings
For external use only

Do not use on broken skin

Ask a doctor before use if you have kidney disease

Stop use if rash or irritation occurs

Keep out of reach of children. If swallowed, get medical help or contact a Poison Control Center right away.

Directions
apply to underarms only

INACTIVE INGREDIENT

Cyclopentasiloxane
PPG-14 Butyl Ether
Stearyl Alcohol
Hydrogenated Castor Oil
PEG-8 Distearate
Talc
Fragrance
Zea Mays (Corn) Starch
BHT

Questions?
Call toll-free 1-866-DEGREE1

PACKAGE LABEL

PDP front 2.7 oz

PACKAGE LABEL

PDP 2.7 oz back